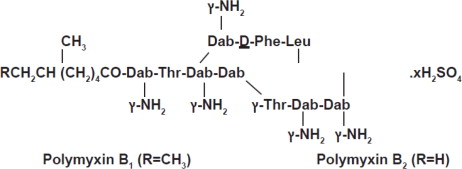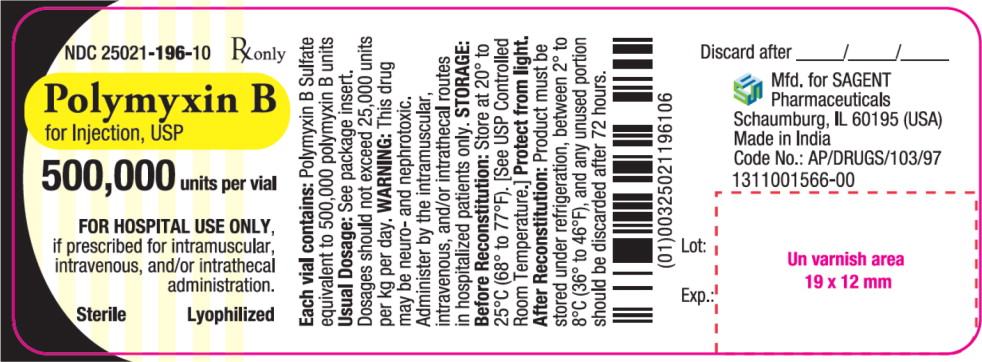 DRUG LABEL: Polymyxin B
NDC: 25021-196 | Form: INJECTION, POWDER, LYOPHILIZED, FOR SOLUTION
Manufacturer: Sagent Pharmaceuticals
Category: prescription | Type: HUMAN PRESCRIPTION DRUG LABEL
Date: 20251001

ACTIVE INGREDIENTS: Polymyxin B Sulfate 500000 [USP'U]/1 1

Polymyxin B for Injection, USP

sagent®
Rx only

To reduce the development of drug-resistant bacteria and maintain the effectiveness of polymyxin B and other antibacterial drugs, polymyxin B should be used only to treat or prevent infections that are proven or strongly suspected to be caused by bacteria.

WARNING

CAUTION: WHEN THIS DRUG IS GIVEN INTRAMUSCULARLY AND/OR INTRATHECALLY, IT SHOULD BE GIVEN ONLY TO HOSPITALIZED PATIENTS, SO AS TO PROVIDE CONSTANT SUPERVISION BY A PHYSICIAN.

RENAL FUNCTION SHOULD BE CAREFULLY DETERMINED AND PATIENTS WITH RENAL DAMAGE AND NITROGEN RETENTION SHOULD HAVE REDUCED DOSAGE. PATIENTS WITH NEPHROTOXICITY DUE TO POLYMYXIN B SULFATE USUALLY SHOW ALBUMINURIA, CELLULAR CASTS, AND AZOTEMIA. DIMINISHING URINE OUTPUT AND A RISING BUN ARE INDICATIONS FOR DISCONTINUING THERAPY WITH THIS DRUG.

NEUROTOXIC REACTIONS MAY BE MANIFESTED BY IRRITABILITY, WEAKNESS, DROWSINESS, ATAXIA, PERIORAL PARESTHESIA, NUMBNESS OF THE EXTREMITIES, AND BLURRING OF VISION. THESE ARE USUALLY ASSOCIATED WITH HIGH SERUM LEVELS FOUND IN PATIENTS WITH IMPAIRED RENAL FUNCTION AND/OR NEPHROTOXICITY.

THE CONCURRENT OR SEQUENTIAL USE OF OTHER NEUROTOXIC AND/OR NEPHROTOXIC DRUGS WITH POLYMYXIN B SULFATE, PARTICULARLY BACITRACIN, STREPTOMYCIN, NEOMYCIN, KANAMYCIN, GENTAMICIN, TOBRAMYCIN, AMIKACIN, CEPHALORIDINE, PAROMOMYCIN, VIOMYCIN, AND COLISTIN SHOULD BE AVOIDED.

THE NEUROTOXICITY OF POLYMYXIN B SULFATE CAN RESULT IN RESPIRATORY PARALYSIS FROM NEUROMUSCULAR BLOCKADE, ESPECIALLY WHEN THE DRUG IS GIVEN SOON AFTER ANESTHESIA AND/OR MUSCLE RELAXANTS.

USAGE IN PREGNANCY: THE SAFETY OF THIS DRUG IN HUMAN PREGNANCY HAS NOT BEEN ESTABLISHED.

DESCRIPTION

Polymyxin B for Injection, USP is one of a group of basic polypeptide antibiotics derived from B. polymyxa (B. aerosporous). Polymyxin B sulfate is the sulfate salt of Polymyxins B1 and B2, which are produced by the growth of Bacillus polymyxa (Prazmowski) Migula (Fam. Bacillacea). It has a potency of not less than 6,000 polymyxin B units per mg, calculated on the anhydrous basis. The structural formulae are:

Each vial contains 500,000 polymyxin B units for parenteral or ophthalmic administration.

Polymyxin B for Injection, USP is in powder form suitable for preparation of sterile solutions for intramuscular, intravenous drip, intrathecal, or ophthalmic use.

In the medical literature, dosages have frequently been given in terms of equivalent weights of pure polymyxin B base. Each milligram of pure polymyxin B base is equivalent to 10,000 units of polymyxin B and each microgram of pure polymyxin B base is equivalent to 10 units of polymyxin B.

Aqueous solutions of polymyxin B sulfate may be stored up to 12 months without significant loss of potency if kept under refrigeration. In the interest of safety, solutions for parenteral use should be stored under refrigeration and any unused portion should be discarded after 72 hours. Polymyxin B sulfate should not be stored in alkaline solutions since they are less stable.

CLINICAL PHARMACOLOGY

Polymyxin B sulfate has a bactericidal action against almost all gram-negative bacilli except the Proteus group. Polymyxins increase the permeability of the bacterial cell membrane leading to death of the cell. All gram-positive bacteria, fungi, and gram-negative cocci are resistant to polymyxin B.

Susceptibility Testing

For specific information regarding susceptibility test interpretive criteria and associated test methods and quality control standards recognized by FDA for this drug, please see: https://www.fda.gov/STIC.

Polymyxin B sulfate is not absorbed from the normal alimentary tract. Since the drug loses 50 percent of its activity in the presence of serum, active blood levels are low. Repeated injections may give a cumulative effect. Levels tend to be higher in infants and children. The drug is excreted slowly by the kidneys. Tissue diffusion is poor and the drug does not pass the blood brain barrier into the cerebrospinal fluid. In therapeutic dosage, polymyxin B sulfate causes some nephrotoxicity with tubule damage to a slight degree.

INDICATIONS AND USAGE

Acute Infections Caused by Susceptible Strains of Pseudomonas aeruginosa

Polymyxin B sulfate is a drug of choice in the treatment of infections of the urinary tract, meninges, and bloodstream caused by susceptible strains of Ps. aeruginosa. It may also be used topically and subconjunctivally in the treatment of infections of the eye caused by susceptible strains of Ps. aeruginosa.

It may be indicated in serious infections caused by susceptible strains of the following organisms, when less potentially toxic drugs are ineffective or contraindicated:

H. influenzae, specifically meningeal infections.

Escherichia coli, specifically urinary tract infections.

Aerobacter aerogenes, specifically bacteremia.

Klebsiella pneumoniae, specifically bacteremia.

NOTE: IN MENINGEAL INFECTIONS, POLYMYXIN B SULFATE SHOULD BE ADMINISTERED ONLY BY THE INTRATHECAL ROUTE.

To reduce the development of drug-resistant bacteria and maintain the effectiveness of polymyxin B and other antibacterial drugs, polymyxin B should be used only to treat or prevent infections that are proven or strongly suspected to be caused by susceptible bacteria. When culture and susceptibility information are available, they should be considered in selecting or modifying antibacterial therapy. In the absence of such data, local epidemiology and susceptibility patterns may contribute to the empiric selection of therapy.

CONTRAINDICATIONS

This drug is contraindicated in persons with a prior history of hypersensitivity reactions to polymyxins.

WARNINGS

Clostridium difficile associated diarrhea (CDAD) has been reported with use of nearly all antibacterial agents, including Polymyxin B for Injection, and may range in severity from mild diarrhea to fatal colitis. Treatment with antibacterial agents alters the normal flora of the colon leading to overgrowth of C. difficile.

C. difficile produces toxins A and B which contribute to the development of CDAD. Hypertoxin producing strains of C. difficile cause increased morbidity and mortality, as these infections can be refractory to antimicrobial therapy and may require colectomy. CDAD must be considered in all patients who present with diarrhea following antibiotic use. Careful medical history is necessary since CDAD has been reported to occur over two months after the administration of antibacterial agents.

If CDAD is suspected or confirmed, ongoing antibiotic use not directed against C. difficile may need to be discontinued. Appropriate fluid and electrolyte management, protein supplementation, antibiotic treatment of C. difficile, and surgical evaluation should be instituted as clinically indicated.

Electrolyte and Acid/Base Abnormalities

Postmarketing cases of renal tubulopathy (i.e., Pseudo-Bartter syndrome) have been identified with the use of intravenous polymyxins, including polymyxin B (see ADVERSE REACTIONS). All cases reported hypokalemia and metabolic alkalosis. Other common findings included hypocalcemia, hypomagnesemia, increased potassium in the urine, normal serum creatinine, and normal blood pressure. Consider electrolyte monitoring during treatment. Normalization of electrolyte abnormalities may require drug discontinuation.

PRECAUTIONS

General

Prescribing polymyxin B in the absence of a proven or strongly suspected bacterial infection or a prophylactic indication is unlikely to provide benefit to the patient and increases the risk of the development of drug-resistant bacteria.

See WARNING box.

Baseline renal function should be done prior to therapy, with frequent monitoring of renal function and blood levels of the drug during parenteral therapy.

Avoid concurrent use of a curariform muscle relaxant and other neurotoxic drugs (ether, tubocurarine, succinylcholine, gallamine, decamethonium and sodium citrate) which may precipitate respiratory depression. If signs of respiratory paralysis appear, respiration should be assisted as required, and the drug discontinued.

As with other antibiotics, use of this drug may result in overgrowth of nonsusceptible organisms, including fungi.

If superinfection occurs, appropriate therapy should be instituted.

Information for Patients

Patients should be counseled that antibacterial drugs including polymyxin B should only be used to treat bacterial infections. They do not treat viral infections (e.g., the common cold). When polymyxin B is prescribed to treat a bacterial infection, patients should be told that although it is common to feel better early in the course of therapy, the medication should be taken exactly as directed. Skipping doses or not completing the full course of therapy may (1) decrease the effectiveness of the immediate treatment and (2) increase the likelihood that bacteria will develop resistance and will not be treatable by polymyxin B or other antibacterial drugs in the future.

Diarrhea is a common problem caused by antibiotics which usually ends when the antibiotic is discontinued. Sometimes after starting treatment with antibiotics, patients can develop watery and bloody stools (with or without stomach cramps and fever) even as late as two or more months after having taken the last dose of the antibiotic. If this occurs, patients should contact their physician as soon as possible.

ADVERSE REACTIONS

See WARNING box.

Nephrotoxic reactions

Albuminuria, cylinduria, azotemia, and rising blood levels without any increase in dosage.

Renal system reactions

Electrolyte and acid/base abnormalities (i.e., Pseudo-Bartter syndrome)

Neurotoxic reactions

Facial flushing, dizziness progressing to ataxia, drowsiness, peripheral paresthesias (circumoral and stocking glove), apnea due to concurrent use of curariform muscle relaxants, other neurotoxic drugs or inadvertent overdosage, and signs of meningeal irritation with intrathecal administration, e.g., fever, headache, stiff neck and increased cell count and protein cerebrospinal fluid.

Other reactions occasionally reported

Drug fever, urticarial rash, pain (severe) at intramuscular injection sites, and thrombophlebitis at intravenous injection sites.

To report SUSPECTED ADVERSE REACTIONS, contact Sagent Pharmaceuticals at 1-866-625-1618 or FDA at 1-800-FDA-1088 or www.fda.gov/medwatch.

DOSAGE AND ADMINISTRATION

PARENTERAL

Intravenous

Dissolve 500,000 polymyxin B units in 300 to 500 mL solutions for parenteral dextrose injection 5% for continuous drip.

Adults and children

15,000 to 25,000 units/kg body weight/day in individuals with normal kidney function. This amount should be reduced from 15,000 units/kg downward for individuals with kidney impairment. Infusions may be given every 12 hours, however, the total daily dose must not exceed 25,000 units/kg/day.

Infants

Infants with normal kidney function may receive up to 40,000 units/kg/day without adverse effects.

Intramuscular

Not recommended routinely because of severe pain at injection sites, particularly in infants and children. Dissolve 500,000 polymyxin B units in 2 mL sterile water for injection or sodium chloride injection or procaine hydrochloride injection 1%.

Adults and children

25,000 to 30,000 units/kg/day. This should be reduced in the presence of renal impairment. The dosage may be divided and given at either 4 or 6 hour intervals.

Infants

Infants with normal kidney function may receive up to 40,000 units/kg/day without adverse effects.

Note: Doses as high as 45,000 units/kg/day have been used in limited clinical studies in treating prematures and newborn infants for sepsis caused by Ps. aeruginosa.

Intrathecal

A treatment of choice for Ps aeruginosa meningitis

Dissolve 500,000 polymyxin B units in 10 mL sodium chloride injection USP for 50,000 units per mL dosage unit.

Adults and children over 2 years of age

Dosage is 50,000 units once daily intrathecally for 3 to 4 days, then 50,000 units once every other day for at least 2 weeks after cultures of the cerebrospinal fluid are negative and sugar content has returned to normal.

Children under 2 years of age

20,000 units once daily, intrathecally for 3 to 4 days or 25,000 units once every other day. Continue with a dose of 25,000 units once every other day for at least 2 weeks after cultures of the cerebrospinal fluid are negative and sugar content has returned to normal.

IN THE INTEREST OF SAFETY, SOLUTIONS OF PARENTERAL USE SHOULD BE STORED UNDER REFRIGERATION, AND ANY UNUSED PORTIONS SHOULD BE DISCARDED AFTER 72 HOURS.

TOPICAL

Ophthalmic

Dissolve 500,000 polymyxin B units in 20 to 50 mL sterile water for injection or sodium chloride injection USP for a 10,000 to 25,000 units per mL concentration.

For the treatment of Ps. aeruginosa infections of the eye, a concentration of 0.1 percent to 0.25 percent (10,000 units to 25,000 units per mL) is administered 1 to 3 drops every hour, increasing the intervals as response indicates.

Subconjunctival injection of up to 100,000 units/day may be used for the treatment of Ps. aeruginosa infections of the cornea and conjunctiva.

Note: Avoid total systemic and ophthalmic instillation over 25,000 units/kg/day.

HOW SUPPLIED

Polymyxin B for Injection, USP is supplied as follows:

NDC | Polymyxin B for Injection, USP | Package Factor
25021-196-10 | 500,000 units per vial | 10 vials per carton

Storage Conditions

Before Reconstitution: Store at 20° to 25°C (68° to 77°F). [See USP Controlled Room Temperature.]

Protect from light. Retain in carton until time of use.

After Reconstitution: Product must be stored under refrigeration, between 2° and 8°C (36° and 46°F), and any unused portion should be discarded after 72 hours.

Lyophilized.

Sterile, Nonpyrogenic, Preservative-free.
The container closure is not made with natural rubber latex.

sagent®
Mfd. for SAGENT Pharmaceuticals
Schaumburg, IL 60173 (USA)
Made in India
©2025 Sagent Pharmaceuticals

Revised: June 2025

PACKAGE LABEL – PRINCIPAL DISPLAY PANEL – Vial Label

NDC 25021-196-10

Rx only

Polymyxin B for Injection, USP

500,000 units per vial

FOR HOSPITAL USE ONLY,

if prescribed for intramuscular, intravenous, and/or intrathecal administration.

Sterile

Lyophilized